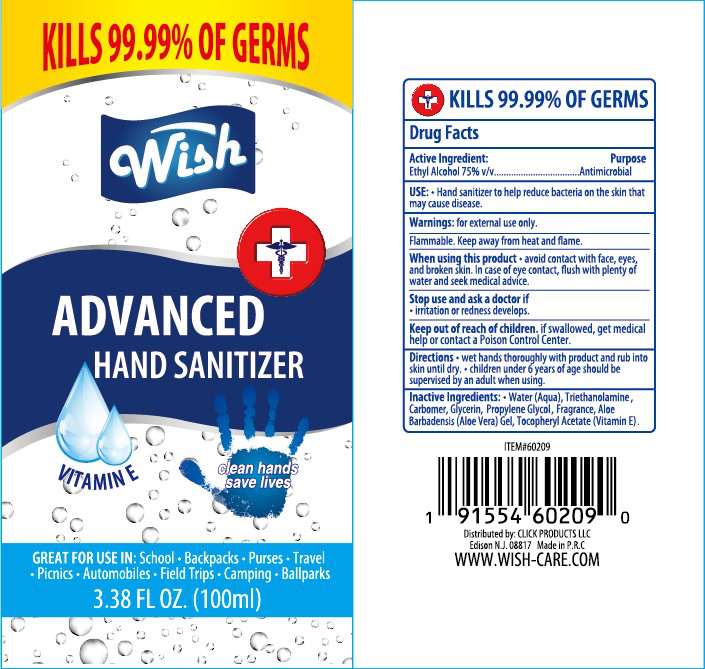 DRUG LABEL: Wish Advanced Hand Sanitizer
NDC: 71611-034 | Form: LIQUID
Manufacturer: Click Products LLC
Category: otc | Type: HUMAN OTC DRUG LABEL
Date: 20200604

ACTIVE INGREDIENTS: ALCOHOL 70.4 mL/100 mL
INACTIVE INGREDIENTS: GLYCERIN 0.5 mL/100 mL; PROPYLENE GLYCOL 0.5 mL/100 mL; TROLAMINE 0.5 mL/100 mL; CARBOMER 940 0.5 mL/100 mL; .ALPHA.-TOCOPHEROL ACETATE 0.05 mL/100 mL; ALOE VERA LEAF 0.05 mL/100 mL; WATER 27.3 mL/100 mL; PAEONIA LACTIFLORA WHOLE 0.2 mL/100 mL

hand sanitizer -02876

Drug facts

Kills 99.9% of germs

Active ingredient

Active Ingredient Purpose

Ethyl Alcohol 75% Antimicrobial

use

Hand sanitizer to help reduce bacterial on skin that potentially can cause disease.

warnings

For External Use Only.

Flammable: Keep away from heat or flame.

When using this product

Avoid contact with face, eyes and broken skin. In case of eye contact, flush with plenty of water and seek medical advice.

Stop and ask a doctor if

irritation or redness develops.

Keep out of reach of children.

If swallowed get immediate medical help or contact a poison contaol center right away.

Directions

DOSAGE AND ADMINISTRATION

Wet hands thoroughly with product and allow to dry without wiping.

USER SAFETY WARNINGS

Children under 6 years of age should be supervised by an adult when using.

Inactive Ingredients:

Water(aqua), Glycerin, Propylene Glycol, Carbomer, Triethanolamine, Fragrance, Aloe Barbadensis(Aloe Vera) Gel, Tocopheryl acetate(vitamin E),